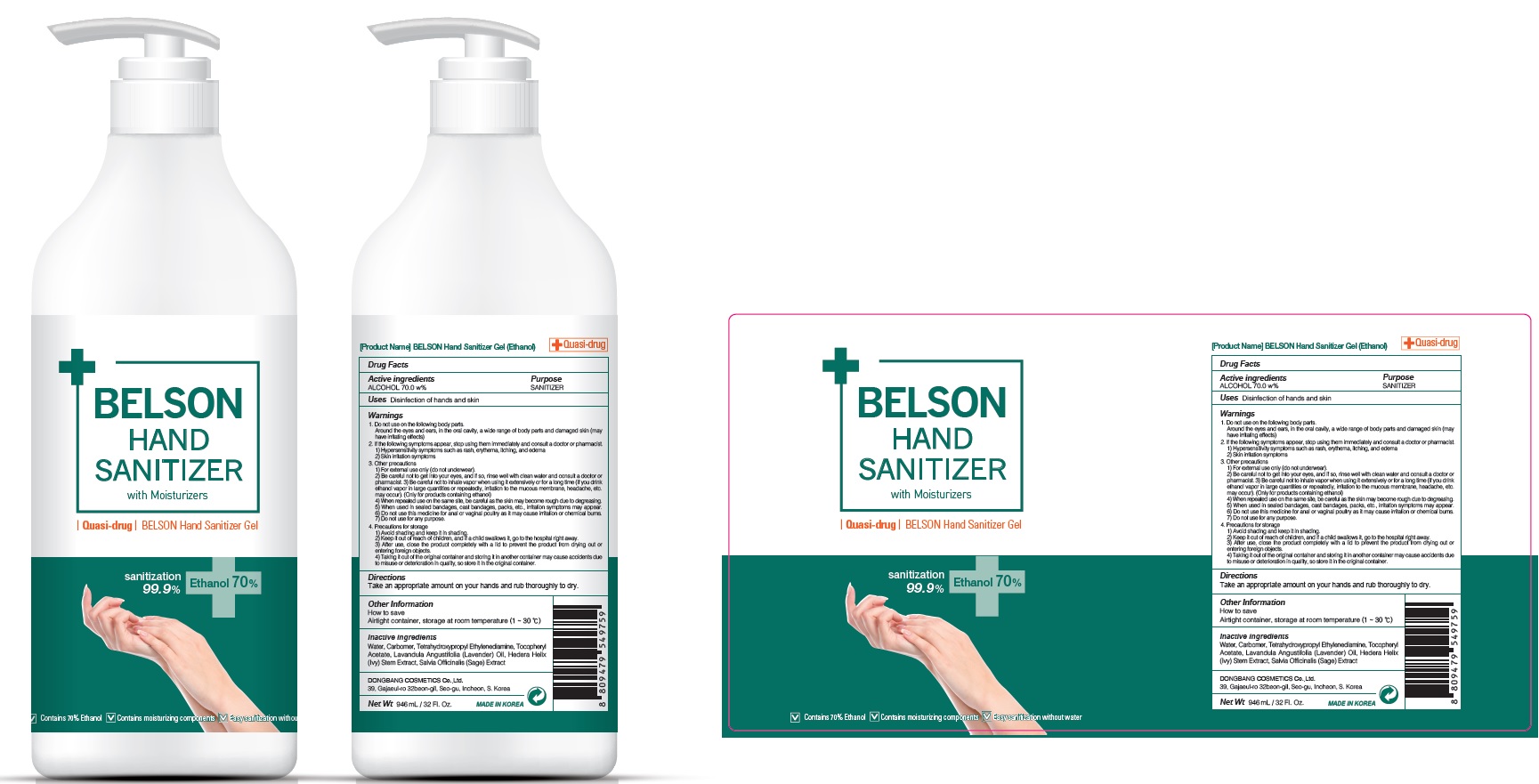 DRUG LABEL: BELSON HAND SANITIZER
NDC: 74002-3050 | Form: GEL
Manufacturer: DONGBANGCOSMETICS CO.,LTD
Category: otc | Type: HUMAN OTC DRUG LABEL
Date: 20200619

ACTIVE INGREDIENTS: ALCOHOL 70 g/100 mL
INACTIVE INGREDIENTS: Water; CARBOMER HOMOPOLYMER, UNSPECIFIED TYPE; EDETOL; .ALPHA.-TOCOPHEROL ACETATE; LAVENDER OIL; HEDERA HELIX LEAF; SALVIA OFFICINALIS ROOT

ACTIVE INGREDIENT

ALCOHOL 70.0 w%

INACTIVE INGREDIENTS

Water, Carbomer, Tetrahydroxypropyl Ethylenediamine, Tocopheryl Acetate, Lavandula Angustifolia (Lavender) Oil, Hedera Helix (Ivy) Stem Extract, Salvia Officinalis (Sage) Extract

PURPOSE

SANITIZER

WARNINGS

1. Do not use on the following body parts.Around the eyes and ears, in the oral cavity, a wide range of body parts and damaged skin (may have irritating effects)

2. If the following symptoms appear, stop using them immediately and consult a doctor or pharmacist.1) Hypersensitivity symptoms such as rash, erythema, itching, and edema2) Skin irritation symptoms
3. Other precautions1) For external use only (do not underwear).2) Be careful not to get into your eyes, and if so, rinse well with clean water and consult a doctor or pharmacist.3) Be careful not to inhale vapor when using it extensively or for a long time (if you drink ethanol vapor in large quantities or repeatedly, irritation to the mucous membrane, headache, etc. may occur). (Only for products containing ethanol) 4) When repeated use on the same site, be careful as the skin may become rough due to degreasing.5) When used in sealed bandages, cast bandages, packs, etc., irritation symptoms may appear.6) Do not use this medicine for anal or vaginal poultry as it may cause irritation or chemical burns.7) Do not use for any purpose.
4. Precautions for storage1) Avoid shading and keep it in shading.2) Keep it out of reach of children, and if a child swallows it, go to the hospital right away.3) After use, close the product completely with a lid to prevent the product from drying out or entering foreign objects.4) Taking it out of the original container and storing it in another container may cause accidents due to misuse or deterioration in quality, so store it in the original container.

KEEP OUT OF REACH OF CHILDREN

Keep it out of reach of children, and if a child swallows it, go to the hospital right away.

Uses

Disinfection of hands and skin

Directions

Take an appropriate amount on your hands and rub thoroughly to dry.

Other lnformation

How to save.
Airtight container, storage at room temperature (1~30°c)